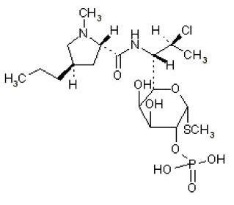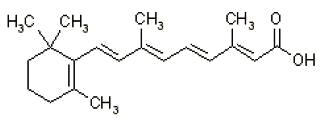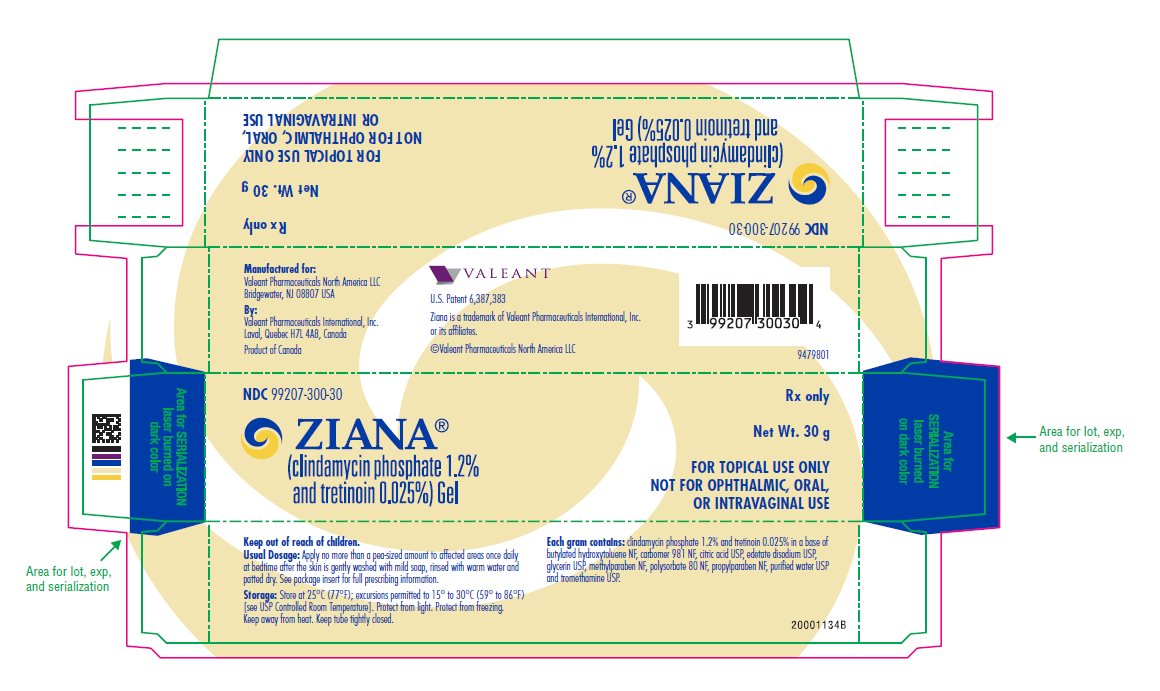 DRUG LABEL: ZIANA
NDC: 99207-300 | Form: GEL
Manufacturer: Bausch Health US, LLC
Category: prescription | Type: HUMAN PRESCRIPTION DRUG LABEL
Date: 20170301

ACTIVE INGREDIENTS: clindamycin phosphate 12 mg/1 g; tretinoin 0.25 mg/1 g
INACTIVE INGREDIENTS: water; glycerin; CARBOMER HOMOPOLYMER TYPE A (ALLYL PENTAERYTHRITOL CROSSLINKED); methylparaben; polysorbate 80; edetate disodium; ANHYDROUS CITRIC ACID; propylparaben; butylated hydroxytoluene; tromethamine

HIGHLIGHTS OF PRESCRIBING INFORMATION

These highlights do not include all the information needed to use ZIANA Gel safely and effectively. See full prescribing information for ZIANA Gel.
ZIANA® (clindamycin phosphate 1.2% and tretinoin 0.025%) Gel
For topical use only
Initial U.S. Approval: 2006

1 INDICATIONS AND USAGE

ZIANA® Gel is a lincosamide antibiotic and retinoid combination product indicated for the topical treatment of acne vulgaris in patients 12 years or older. (1)

2 DOSAGE AND ADMINISTRATION

- Apply a pea-sized amount to the entire face once daily at bedtime. Do not apply to eyes, mouth, angles of the nose, or mucous membranes. (2)
- ZIANA Gel is not for oral, ophthalmic, or intravaginal use. (2)

3 DOSAGE FORMS AND STRENGTHS

Topical gel: Clindamycin phosphate 1.2% and tretinoin 0.025% gel in 30 and 60 gram tubes. (3)

4 CONTRAINDICATIONS

ZIANA Gel is contraindicated in patients with regional enteritis, ulcerative colitis, or history of antibiotic–associated colitis. (4)

5 WARNINGS AND PRECAUTIONS

- Colitis: Clindamycin can cause severe colitis, which may result in death. Diarrhea, bloody diarrhea, and colitis (including pseudomembranous colitis) have been reported with the use of clindamycin. ZIANA Gel should be discontinued if significant diarrhea occurs. (5.1)
- Ultraviolet Light and Environmental Exposures: Avoid exposure to sunlight and sunlamps. Wear sunscreen daily. (5.2)

6 ADVERSE REACTIONS

Observed local adverse reactions in patients treated with ZIANA Gel were skin erythema, scaling, itching, burning, and stinging. Other most commonly reported adverse events (≥1% in patients treated with ZIANA Gel) were nasopharyngitis, pharyngolaryngeal pain, dry skin, cough, and sinusitis. (6.1)

To report SUSPECTED ADVERSE REACTIONS, contact Valeant Pharmaceuticals North America LLC at 1-800-321-4576 or FDA at 1-800-FDA-1088 or www.fda.gov/medwatch

7 DRUG INTERACTIONS

- Concomitant use of topical medications with a strong drying effect can increase skin irritation. Use with caution. (7.1)
- ZIANA Gel should not be used in combination with erythromycin-containing products because of its clindamycin component. (7.2)

FULL PRESCRIBING INFORMATION

1 INDICATIONS AND USAGE

ZIANA Gel is indicated for the topical treatment of acne vulgaris in patients 12 years or older.

2 DOSAGE AND ADMINISTRATION

At bedtime, squeeze a pea-sized amount of medication onto one fingertip, dot onto the chin, cheeks, nose, and forehead, then gently rub over the entire face. ZIANA Gel should be kept away from the eyes, the mouth, angles of the nose, and mucous membranes.

ZIANA Gel is not for oral, ophthalmic, or intravaginal use.

3 DOSAGE FORMS AND STRENGTHS

ZIANA Gel, a combination of a lincosamide antibiotic and a retinoid, contains clindamycin phosphate 1.2% and tretinoin 0.025%, formulated as a topical gel. Each gram of ZIANA Gel contains, as dispensed, 10 mg (1%) clindamycin as phosphate, and 0.25 mg (0.025%) tretinoin in an aqueous-based gel. ZIANA Gel is available in 30 gram and 60 gram tubes.

4 CONTRAINDICATIONS

ZIANA Gel is contraindicated in patients with regional enteritis, ulcerative colitis, or history of antibiotic-associated colitis.

5 WARNINGS AND PRECAUTIONS

5.1 Colitis

Systemic absorption of clindamycin has been demonstrated following topical use of this product. Diarrhea, bloody diarrhea, and colitis (including pseudomembranous colitis) have been reported with the use of topical clindamycin. When significant diarrhea occurs, ZIANA Gel should be discontinued.

Severe colitis has occurred following oral or parenteral administration of clindamycin with an onset of up to several weeks following cessation of therapy. Antiperistaltic agents such as opiates and diphenoxylate with atropine may prolong and/or worsen severe colitis. Severe colitis may result in death.

Studies indicate a toxin(s) produced by clostridia is one primary cause of antibiotic-associated colitis. The colitis is usually characterized by severe persistent diarrhea and severe abdominal cramps and may be associated with the passage of blood and mucus. Stool cultures for Clostridium difficile and stool assay for C. difficile toxin may be helpful diagnostically.

5.2 Ultraviolet Light and Environmental Exposure

Exposure to sunlight, including sunlamps, should be avoided during the use of ZIANA Gel, and patients with sunburn should be advised not to use the product until fully recovered because of heightened susceptibility to sunlight as a result of the use of tretinoin. Patients who may be required to have considerable sun exposure due to occupation and those with inherent sensitivity to the sun should exercise particular caution. Daily use of sunscreen products and protective apparel (e.g., a hat) are recommended. Weather extremes, such as wind or cold, also may be irritating to patients under treatment with ZIANA Gel.

6 ADVERSE REACTIONS

6.1 Clinical Studies Experience

Because clinical trials are conducted under prescribed conditions, adverse reaction rates observed in the clinical trial may not reflect the rates observed in practice. The adverse reaction information from clinical trials does, however, provide a basis for identifying the adverse reactions that appear to be related to drug use for approximating rates.

The safety data presented in Table 1 (below) reflects exposure to ZIANA Gel in 1853 patients with acne vulgaris. Patients were 12 years and older and were treated once daily for 12 weeks. Adverse reactions that were reported in ≥1% of patients treated with ZIANA Gel were compared to adverse reactions in patients treated with clindamycin phosphate 1.2% in vehicle gel, tretinoin 0.025% in vehicle gel, and the vehicle gel alone:

Table 1: Adverse Reactions Reported in at Least 1% of Patients Treated with ZIANA Gel: 12-Week Studies
 | ZIANA Gel N=1853 N (%) | Clindamycin N=1428 N (%) | Tretinoin N=846 N (%) | Vehicle N=423 N (%)
PATIENTS WITH AT LEAST ONE AR | 497 (27) | 342 (24) | 225 (27) | 91 (22)
Nasopharyngitis | 65 (4) | 64 (5) | 16 (2) | 5 (1)
Pharyngolaryngeal pain | 29 (2) | 18 (1) | 5 (1) | 7 (2)
Dry skin | 23 (1) | 7 (1) | 3 (<1) | 0 (0)
Cough | 19 (1) | 21 (2) | 9 (1) | 2 (1)
Sinusitis | 19 (1) | 19 (1) | 15 (2) | 4 (1)
NOTE: Formulations used in all treatment arms were in the ZIANA vehicle gel.

Cutaneous safety and tolerance evaluations were conducted at each study visit in all of the clinical trials by assessment of erythema, scaling, itching, burning, and stinging:

Table 2: ZIANA Gel-Treated Patients with Local Skin Reactions
Local Reaction | Baseline N=1835 N (%) | End of Treatment N=1614 N (%)
Erythema | 636 (35) | 416 (26)
Scaling | 237 (13) | 280 (17)
Itching | 189 (10) | 70 (4)
Burning | 38 (2) | 56 (4)
Stinging | 33 (2) | 27 (2)

At each study visit, application site reactions on a scale of 0 (none), 1 (mild), 2 (moderate), and 3 (severe), and the mean scores were calculated for each of the local skin reactions. In Studies 1 and 2, 1277 subjects enrolled with moderate to severe acne, 854 subjects treated with ZIANA Gel and 423 treated with vehicle. Analysis over the 12-week period demonstrated that cutaneous irritation scores for erythema, scaling, itching, burning, and stinging peaked at 2 weeks of therapy, and were slightly higher for the ZIANA-treated group, decreasing thereafter.

One open-label 12-month safety study for ZIANA Gel showed a similar adverse reaction profile as seen in the 12-week studies. Eighteen out of 442 subjects (4%) reported gastrointestinal symptoms.

7 DRUG INTERACTIONS

7.1 Concomitant Topical Medication

Concomitant topical medication, medicated or abrasive soaps and cleansers, soaps and cosmetics that have a strong drying effect, and products with high concentrations of alcohol, astringents, spices or lime should be used with caution. When used with ZIANA Gel, there may be increased skin irritation.

7.2 Erythromycin

ZIANA Gel should not be used in combination with erythromycin-containing products due to its clindamycin component. In vitro studies have shown antagonism between these two antimicrobials. The clinical significance of this in vitro antagonism is not known.

7.3 Neuromuscular Blocking Agents

Clindamycin has been shown to have neuromuscular blocking properties that may enhance the action of other neuromuscular blocking agents. Therefore, ZIANA Gel should be used with caution in patients receiving such agents.

8 USE IN SPECIFIC POPULATIONS

8.1 Pregnancy

TERATOGENIC EFFECTS

Pregnancy Category C. There are no well-controlled trials in pregnant women treated with ZIANA Gel. ZIANA Gel should be used during pregnancy only if the potential benefit justifies the potential risk to the fetus. ZIANA Gel was tested for maternal and developmental toxicity in New Zealand White Rabbits with topical doses of 60, 180 and 600 mg/kg/day. ZIANA Gel at 600 mg/kg/day (approximately 12 times the recommended clinical dose assuming 100% absorption and based on body surface area comparison) was considered to be the no-observed-adverse-effect level (NOAEL) for maternal and developmental toxicity following dermal administration of ZIANA Gel for 2 weeks prior to artificial insemination and continuing until gestation day 18, inclusive. For purposes of comparisons of the animal exposure to human exposure, the recommended clinical dose is defined as 1 g of ZIANA Gel applied daily to a 60 kg person.

Clindamycin

Teratology (Segment II) studies using clindamycin were performed orally in rats (up to 600 mg/kg/day) and mice (up to 100 mg/kg/day) (583 and 49 times amount of clindamycin in the recommended clinical dose based on body surface area comparison, respectively) or with subcutaneous doses of clindamycin up to 180 mg/kg/day (175 and 88 times the amount of clindamycin in the recommended clinical dose based on body surface area comparison, respectively) revealed no evidence of teratogenicity.

Tretinoin

In oral Segment III studies in rats with tretinoin, decreased survival of neonates and growth retardation were observed at doses in excess of 2 mg/kg/day (~78 times the recommended clinical dose assuming 100% absorption and based on body surface area comparison).

With widespread use of any drug, a small number of birth defect reports associated temporally with the administration of the drug would be expected by chance alone. Thirty cases of temporally associated congenital malformations have been reported during two decades of clinical use of another formulation of topical tretinoin. Although no definite pattern of teratogenicity and no causal association have been established from these cases, five of the reports describe the rare birth defect category, holoprosencephaly (defects associated with incomplete midline development of the forebrain). The significance of these spontaneous reports in terms of risk to the fetus is not known.

Dermal tretinoin has been shown to be fetotoxic in rabbits when administered in doses 40 times the recommended human clinical dose based on body surface area comparison. Oral tretinoin has been shown to be fetotoxic in rats when administered in doses 78 times the recommended clinical dose based on body surface area comparison.

8.3 Nursing Mothers

It is not known whether clindamycin is excreted in human milk following use of ZIANA Gel. However, orally and parenterally administered clindamycin has been reported to appear in breast milk. Because of the potential for serious adverse reactions in nursing infants, a decision should be made whether to discontinue nursing or to discontinue the drug, taking into account the importance of the drug to the mother. It is not known whether tretinoin is excreted in human milk. Because many drugs are excreted in human milk, caution should be exercised when ZIANA Gel is administered to a nursing woman.

8.4 Pediatric Use

Safety and effectiveness of ZIANA Gel in pediatric patients under the age of 12 have not been established.

Clinical trials of ZIANA Gel included patients 12–17 years of age. [See Clinical Studies (14).]

8.5 Geriatric Use

Clinical studies of ZIANA Gel did not include sufficient numbers of subjects aged 65 and over to determine whether they respond differently from younger subjects.

11 DESCRIPTION

ZIANA (clindamycin phosphate 1.2% and tretinoin 0.025%) Gel is an antibiotic and retinoid combination gel product with two active ingredients. Clindamycin phosphate is a water-soluble ester of the semi-synthetic antibiotic produced by a 7(S)-chloro-substitution of the 7(R)-hydroxyl group of the parent antibiotic lincomycin.

The chemical name for clindamycin phosphate is Methyl 7-chloro-6,7,8-trideoxy-6-(1-methyl-trans-4-propyl-L-2-pyrrolidinecarboxamido)-1-thio-L-threo-α-D-galacto-octopyranoside 2-(dihydrogen phosphate). The structural formula for clindamycin phosphate is represented below:

Clindamycin phosphate:
Molecular Formula: C18H34ClN2O8PS Molecular Weight: 504.97

The chemical name for tretinoin is 3,7-Dimethyl-9-(2,6,6-trimethyl-1-cyclohexen-1-yl)-2,4,6,8 nonatetraenoic acid (all-trans form). The structural formula for tretinoin is represented below:

Tretinoin:

Molecular Formula: C20H28O2 Molecular Weight: 300.44

ZIANA Gel contains the following inactive ingredients: butylated hydroxytoluene NF, carbomer 981 NF, citric acid USP, edetate disodium USP, glycerin USP, methylparaben NF, polysorbate 80 NF, propylparaben NF, purified water USP and tromethamine USP.

12 CLINICAL PHARMACOLOGY

12.1 Mechanisms of Action

Clindamycin

[See Microbiology (12.4).]

Tretinoin

Although the exact mode of action of tretinoin is unknown, current evidence suggests that topical tretinoin decreases cohesiveness of follicular epithelial cells with decreased microcomedo formation.

Additionally, tretinoin stimulates mitotic activity and increased turnover of follicular epithelial cells causing extrusion of the comedones.

12.3 Pharmacokinetics

In an open-label, multiple-dose study treating 12 subjects with moderate to severe acne, the percutaneous absorption of tretinoin following 14 consecutive daily applications of approximately 4 g of ZIANA Gel was minimal. Quantifiable tretinoin plasma concentrations ranged from 1.0 to 1.6 ng/mL, with unquantifiable plasma concentrations in 50% to 92% of subjects at any given timepoint following administration. The plasma concentrations of the key tretinoin metabolites, 13-cis-retinoic acid and 4-oxo-13-cis-retinoic acid, ranged from 1.0 to 1.4 ng/mL and from 1.6 to 6.5 ng/mL, respectively. Plasma concentrations for clindamycin generally did not exceed 3.5 ng/mL, with the exception of one subject whose plasma concentration reached 13.1 ng/mL.

12.4 Microbiology

Clindamycin binds to the 50S ribosomal subunits of susceptible bacteria and prevents elongation of peptide chains by interfering with peptidyl transfer, thereby suppressing bacterial protein synthesis. Clindamycin has been shown to have in vitro activity against Propionibacterium acnes, an organism which has been associated with acne vulgaris; however, the clinical significance of this activity against P. acnes was not examined in clinical trials with ZIANA Gel. P. acnes resistance to clindamycin has been documented. Resistance to clindamycin is often associated with resistance to erythromycin.

13 NONCLINICAL TOXICOLOGY

13.1 Carcinogenesis, Mutagenesis, Impairment of Fertility

Carcinogenicity, mutagenicity and impairment of fertility testing of ZIANA Gel have not been performed in any species.

Clindamycin

The carcinogenicity of a 1% clindamycin phosphate gel similar to ZIANA Gel was evaluated by daily application to mice for 2 years. The daily doses used in this study were approximately 13 and 72 times higher than the human dose of clindamycin phosphate from ZIANA Gel, assuming complete absorption and based on body surface area comparison. No significant increase in tumors was noted in the treated animals. For purposes of comparisons of the animal exposure to human exposure, the recommended human topical clinical dose is defined as 1 g of ZIANA Gel applied daily to a 60 kg person.

Fertility (Segment 1) studies in rats treated orally with up to 300 mg/kg/day of clindamycin (approximately 290 times the amount of clindamycin delivered from the recommended clinical dose for ZIANA Gel, based on body surface area comparison) revealed no effects on fertility or mating ability.

Tretinoin

In two independent studies with long-term topical application of tretinoin in mice, carcinogenicity was not observed. In both studies, tretinoin was administered topically (0.025% or 0.1%) three times per week for up to 2 years. No carcinogenicity was observed with maximum effects of dermal amyloidosis in the basal layer of the skin.

Tretinoin has been shown to enhance photo co-carcinogenicity in properly performed specific studies, employing concurrent or intercurrent exposure to the drug and UV radiation. The contribution of clindamycin to that effect is unknown. Although the significance of these studies to humans is not clear, patients should minimize exposure to sun.

The genotoxic potential of tretinoin was evaluated in an in vitro Ames Salmonella reversion test and an in vitro chromosomal aberration assay in Chinese hamster ovary cells. Both tests were negative.

In oral Segment 1 studies in rats treated with tretinoin, the no-observed-effect-level was 2 mg/kg/day (~78 times the recommended clinical dose assuming 100% absorption and based on body surface area comparison).

14 CLINICAL STUDIES

The safety and efficacy of once daily use of ZIANA Gel for treatment of acne vulgaris were assessed in three 12-week prospective, multi-center, randomized, blinded studies in patients 12 years and older. Studies 1 and 2 were of identical design, and compared ZIANA Gel to clindamycin in the vehicle gel, tretinoin in the vehicle gel, and the vehicle gel alone. Patients with mild, moderate, or severe acne were enrolled in the studies. The co-primary efficacy variables were:

1. Mean percent change from baseline at Week 12 in
  1. inflammatory lesion counts,
  2. non-inflammatory lesion counts, and
  3. total lesion counts
2. Percent of subjects who cleared or almost cleared at Week 12 as judged by an Evaluator's Global Severity (EGS) score.

The EGS scoring scale used in all of the clinical trials for ZIANA Gel is as follows:

Grade | Description
Clear | Normal, clear skin with no evidence of acne vulgaris
Almost Clear | Rare non-inflammatory lesions present, with rare non-inflamed papules (papules must be resolving and may be hyperpigmented, though not pink-red)
Mild | Some non-inflammatory lesions are present, with few inflammatory lesions (papules/pustules only; no nodulocystic lesions)
Moderate | Non-inflammatory lesions predominate, with multiple inflammatory lesions evident: several to many comedones and papules/pustules, and there may or may not be one small nodulo-cystic lesion
Severe | Inflammatory lesions are more apparent, many comedones and papules/pustules, there may or may not be a few nodulocystic lesions
Very Severe | Highly inflammatory lesions predominate, variable number of comedones, many papules/pustules and many nodulocystic lesions

In Study 1, a total of 1252 patients were enrolled, and in Study 2, a total of 1288 patients were enrolled. The combined results are presented in Table 3.

Table 3: Efficacy Results at Week 12 in Studies 1 and 2
 | ZIANA Gel N=845 | Clindamycin N=426 | Tretinoin N=846 | Vehicle N=423
Evaluator's Global Severity: N (%)
Patients achieving success [Success was defined as cleared or almost cleared at Week 12.] | 180 (21%) | 70 (16%) | 122 (14%) | 34 (8%)
Inflammatory Lesion Count (% reduction from baseline)
Mean | 48% | 42% | 39% | 26%
Non-inflammatory Lesion Count (% reduction from baseline)
Mean | 36% | 27% | 31% | 16%
Total Lesion Count (% reduction from baseline)
Mean | 41% | 34% | 34% | 20%

In Study 3, ZIANA Gel was compared to clindamycin gel in a total of 2010 patients with moderate or severe acne vulgaris (see TABLE 3). As with Studies 1 and 2, the co-primary endpoints were mean percent reduction in lesion counts (inflammatory, non-inflammatory and total) and the EGS score. In Study 3, success on the EGS score was assessed by the percentage of subjects who had at least 2 grades of improvement from Baseline to Week 12.

Table 4: Efficacy Results at Week 12 in Study 3
 | ZIANA Gel N=1008 | Clindamycin N=1002
Evaluator's Global Severity: N (%)
Patients achieving success [Success was defined as at least a 2-grade improvement at Week 12 from baseline.] | 415 (41%) | 345 (34%)
Inflammatory Lesion Count (% reduction from baseline)
Mean | 61% | 55%
Non-inflammatory Lesion Count (% reduction from baseline)
Mean | 50% | 41%
Total Lesion Count (% reduction from baseline)
Mean | 54% | 47%

16 HOW SUPPLIED/STORAGE AND HANDLING

ZIANA® (clindamycin phosphate 1.2% and tretinoin 0.025%) Gel is supplied as follows:

30 gram tube NDC 99207-300-30
  60 gram tube NDC 99207-300-60

Storage and Handling

- Store at 25°C (77°F); excursions permitted to 15° to 30°C (59° to 86°F) [see USP Controlled Room Temperature].
- Protect from light.
- Protect from freezing.
- Keep out of the reach of children.
- Keep away from heat.
- Keep tube tightly closed.

17 PATIENT COUNSELING INFORMATION

Advise the patient to read the FDA-approved patient labeling (Patient Information).

Instructions for Use

- At bedtime, the face should be gently washed with a mild soap and warm water. After patting the skin dry, apply ZIANA Gel as a thin layer over the entire face (excluding the eyes and lips).
- Patients should be advised not to use more than the recommended pea-sized amount and not to apply more often than once daily (at bedtime) as this will not make for faster results and may increase irritation.
- A sunscreen should be applied every morning and reapplied over the course of the day as needed. Patients should be advised to avoid exposure to sunlight, sunlamp, ultraviolet light, and other medicines that may increase sensitivity to sunlight.

Skin Irritation

ZIANA Gel may cause irritation such as erythema, scaling, itching, burning, or stinging.

Colitis

In the event a patient treated with ZIANA Gel experiences severe diarrhea or gastrointestinal discomfort, ZIANA Gel should be discontinued and a physician should be contacted.

Manufactured for:
Valeant Pharmaceuticals North America LLC
Bridgewater, NJ 08807 USA

By:
Valeant Pharmaceuticals International, Inc.
Laval, Quebec H7L 4A8, Canada
U.S. Patent 6,387,383

Ziana is a trademark of Valeant Pharmaceuticals International, Inc. or its affiliates.

©Valeant Pharmaceuticals North America LLC

9480201

20001130B

PATIENT INFORMATION
ZIANA® (ZEE-AH-NA)
(clindamycin phosphate 1.2% and tretinoin 0.025%) Gel

IMPORTANT: Not for mouth, eye, or vaginal use.

Read the Patient Information that comes with ZIANA Gel before you start using it and each time you get a refill. There may be new information. This leaflet does not take the place of talking with your doctor about your acne or treatment.

What is ZIANA Gel?

ZIANA Gel is an antibiotic and retinoid combination medicine used for the skin treatment of acne in patients 12 years and older.

Who should not use ZIANA Gel?

Do not use ZIANA Gel if you:

- have Crohn's Disease
- have Ulcerative Colitis
- have developed colitis with past antibiotic use

Tell your doctor:

- if you are pregnant or planning to become pregnant. It is not known if ZIANA Gel may harm your unborn baby.
- if you are breastfeeding. ZIANA Gel may pass through your milk and may harm your baby.
- about all the medicines and skin products you use:
  - ZIANA Gel should not be used with erythromycin-containing products.
  - Avoid medicated or abrasive soaps and cleansers, soaps and cosmetics that have a strong drying effect, and skin products that contain alcohol, astringents, spices or lime. These products may cause increased skin irritation if used with ZIANA Gel.

How should I use ZIANA Gel?

Use ZIANA Gel exactly as prescribed. It may take some time for you to see improvement of your acne with ZIANA Gel. Your doctor will tell you how long to use ZIANA Gel.

At bedtime:

- Wash your face gently with a mild soap and warm water.
- Pat the skin dry.
- Apply a pea-size amount of ZIANA Gel to your fingertip and spread it over your face. Gently, smooth it into your skin. Do not get ZIANA Gel in your eyes or mouth, on your lips, on the corners of your nose, or on open wounds.

In the morning:

- Apply a sunscreen and reapply during the day as needed.
- Do not apply ZIANA Gel more than once a day.
- Do not use too much ZIANA Gel. Too much ZIANA Gel may irritate your skin.
- Do not wash your face more than 2 to 3 times a day. Washing your face too often or scrubbing it may make your acne worse.

Avoid:

- excessive exposure to the sun, cold, and wind. Weather extremes can dry and burn the skin. Always use a sunscreen on ZIANA Gel treated skin, even on cloudy days. Use other protective clothing such as a hat when you are in the sun.
- the use of sunlamps and tanning booths.

If your face becomes sunburned, stop ZIANA Gel until your skin has healed.

What are possible side effects with ZIANA Gel?

- Skin irritation. ZIANA Gel may cause skin irritation such as dryness, redness, peeling, burning, or stinging. Stop ZIANA Gel and call your doctor if your skin becomes very red, swollen, blistered, or crusted.
- Change in skin color. ZIANA Gel may cause a temporary skin color change (lighter or darker).
- Colitis. This occurs rarely. Stop ZIANA Gel and call your doctor if you develop severe watery diarrhea, or bloody diarrhea.

Talk to your doctor about any side effect that bothers you or that does not go away.

These are not all the side effects with ZIANA Gel. Ask your doctor or pharmacist for more information.

How should I store ZIANA Gel?

- Store ZIANA Gel at room temperature, 59° to 86°F (15° to 30°C). Do not freeze.
- Keep ZIANA Gel away from heat and light.
- Keep the tube tightly closed.
- Keep ZIANA Gel and all medicines out of reach of children.

General information about ZIANA Gel

Medicines are sometimes prescribed for purposes other than those listed in patient information leaflet. Do not use ZIANA Gel for a condition for which it was not prescribed. Do not give ZIANA Gel to other people, even if they have the same symptoms you have. It may harm them.

This leaflet summarizes the most important information about ZIANA Gel. If you would like more information, talk with your doctor. You can also ask your pharmacist or doctor for information about ZIANA Gel that is written for healthcare professionals.

If you have questions about ZIANA Gel you can also call: 1-800-321-4576 (this is a toll-free number) between 10:00 a.m. and 4:00 p.m. Eastern Time, Monday through Friday.

What are the ingredients in ZIANA Gel?

Active Ingredients: clindamycin phosphate 1.2% and tretinoin 0.025%

Inactive Ingredients: butylated hydroxytoluene NF, carbomer 981 NF, citric acid USP, edetate disodium USP, glycerin USP, methylparaben NF, polysorbate 80 NF, propylparaben NF, purified water USP and tromethamine USP.

Manufactured for:
Valeant Pharmaceuticals North America LLC
Bridgewater, NJ 08807 USA

By:
Valeant Pharmaceuticals International, Inc.
Laval, Quebec H7L 4A8, Canada

U.S. Patent 6,387,383

Ziana is a trademark of Valeant Pharmaceuticals International, Inc. or its affiliates.

©Valeant Pharmaceuticals North America LLC

9480201
20001130B

Revised: 03/2017

PACKAGE LABEL

PRINCIPAL DISPLAY PANEL - 30 g Carton

NDC 99207-300-30

ZIANA®
(clindamycin phosphate 1.2%
and tretinoin 0.025%) Gel

Rx only

Net Wt. 30 g

FOR TOPICAL USE ONLY
NOT FOR OPHTHALMIC, ORAL,
OR INTRAVAGINAL USE